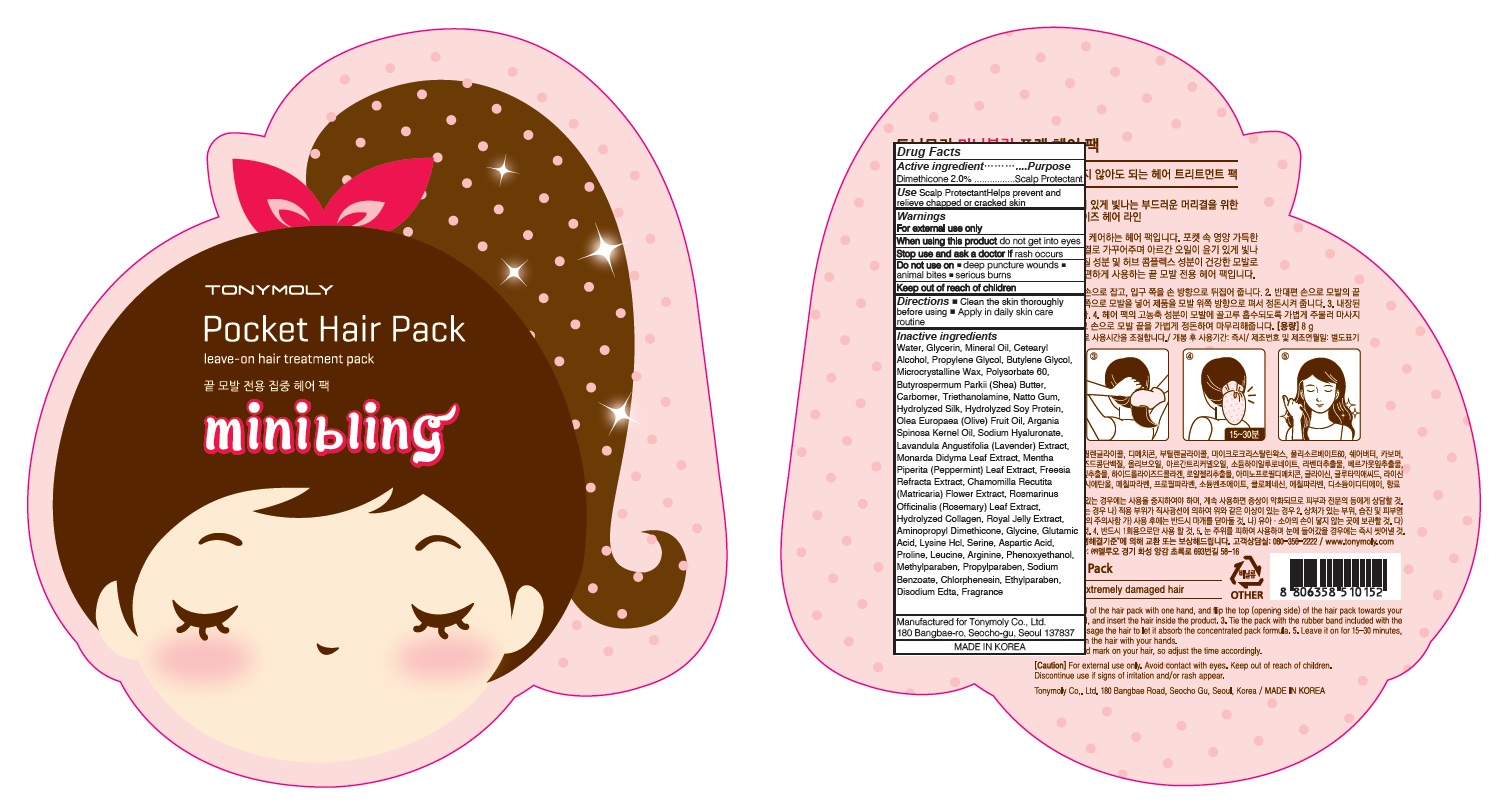 DRUG LABEL: MINI BLING POCKET HAIR PACK
NDC: 59078-321 | Form: PATCH
Manufacturer: TONYMOLY CO.,LTD
Category: otc | Type: HUMAN OTC DRUG LABEL
Date: 20160919

ACTIVE INGREDIENTS: DIMETHICONE 0.16 g/8 g
INACTIVE INGREDIENTS: WATER; GLYCERIN

ACTIVE INGREDIENT

Active Ingredient: DIMETHICONE 2.0%

INACTIVE INGREDIENT

Inactive Ingredients: WATER, GLYCERIN, MINERAL OIL, CETEARYL ALCOHOL, PROPYLENE GLYCOL, BUTYLENE GLYCOL, MICROCRYSTALLINE WAX, POLYSORBATE 60, BUTYROSPERMUM PARKII (SHEA) BUTTER, CARBOMER, TRIETHANOLAMINE, NATTO GUM, HYDROLYZED SILK, HYDROLYZED SOY PROTEIN, OLEA EUROPAEA (OLIVE) FRUIT OIL, ARGANIA SPINOSA KERNEL OIL, SODIUM HYALURONATE, LAVANDULA ANGUSTIFOLIA (LAVENDER) EXTRACT, MONARDA DIDYMA LEAF EXTRACT, MENTHA PIPERITA (PEPPERMINT) LEAF EXTRACT, FREESIA REFRACTA EXTRACT, CHAMOMILLA RECUTITA (MATRICARIA) FLOWER EXTRACT, ROSMARINUS OFFICINALIS (ROSEMARY) LEAF EXTRACT, HYDROLYZED COLLAGEN, ROYAL JELLY EXTRACT, AMINOPROPYL DIMETHICONE, GLYCINE, GLUTAMIC ACID, LYSINE HCL, SERINE, ASPARTIC ACID, PROLINE, LEUCINE, ARGININE, PHENOXYETHANOL, METHYLPARABEN, PROPYLPARABEN, SODIUM BENZOATE, CHLORPHENESIN, ETHYLPARABEN, DISODIUM EDTA, FRAGRANCE

PURPOSE

Purpose: Scalp Protectant

WARNINGS

Warnings: For external use only When using this product do not get into eyes, Stop use and ask a doctor if rash occurs Do not use on - deep puncture wounds - animal bites - serious burns Keep out of reach of children

KEEP OUT OF REACH OF CHILDREN

Use

Use: Helps prevent and relieve chapped or cracked skin

Directions

Directions: - Clean the skin thoroughly before using - Apply in daily skin care routine